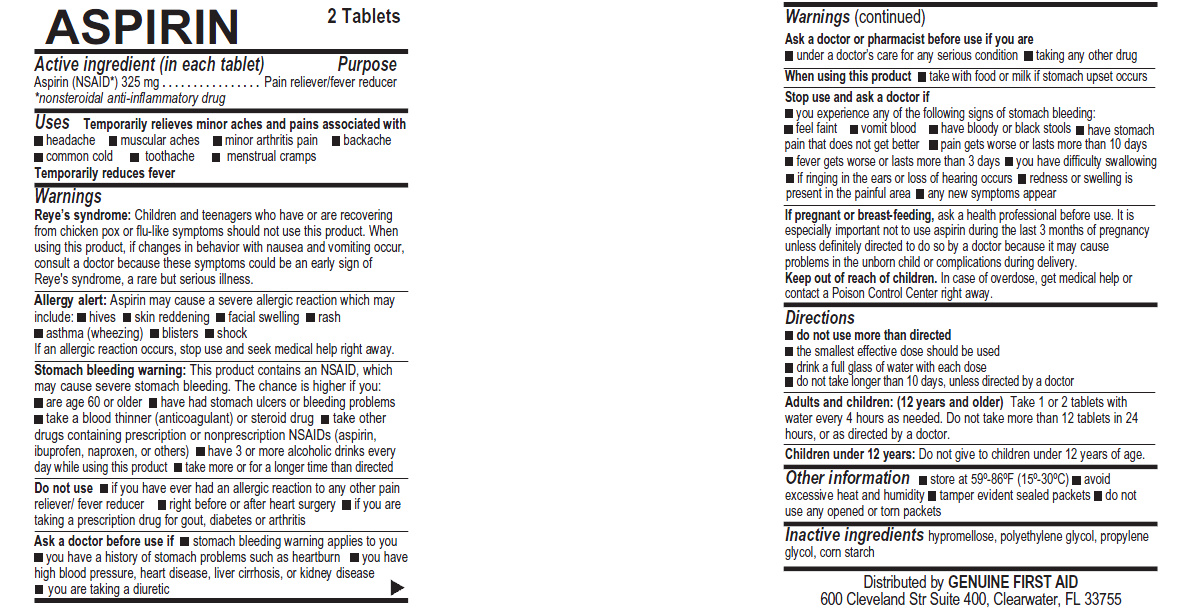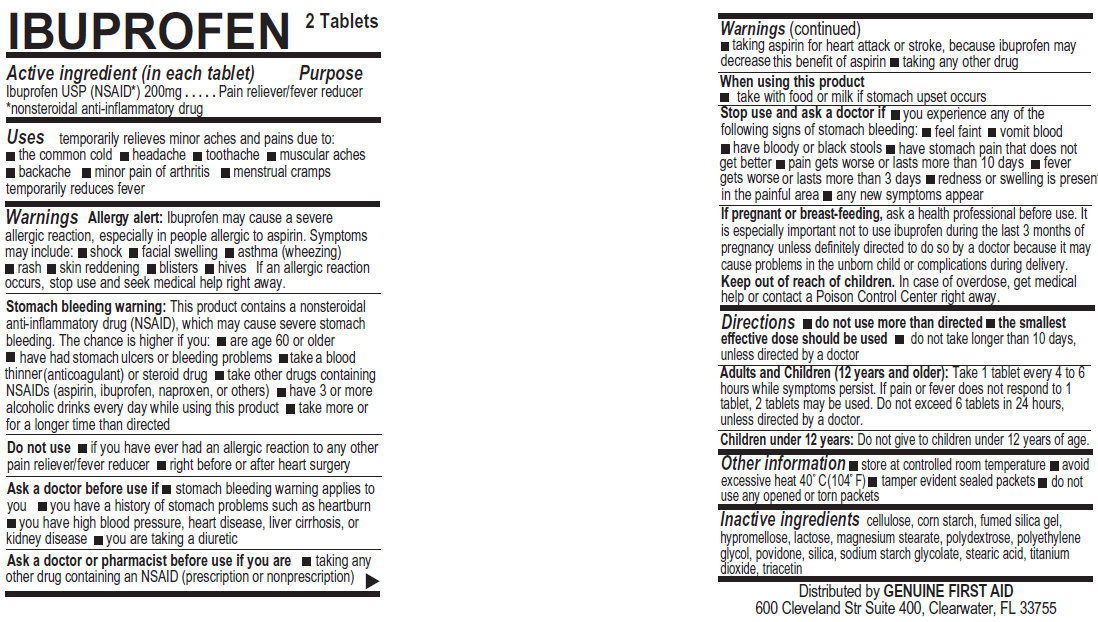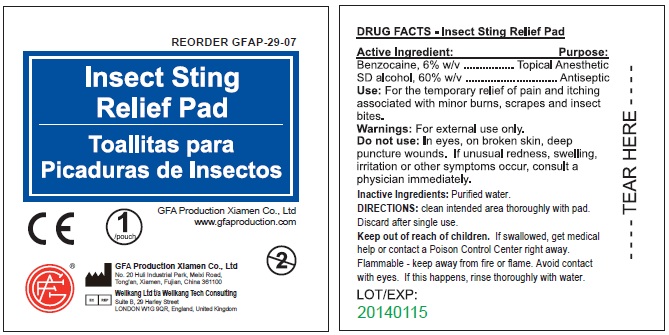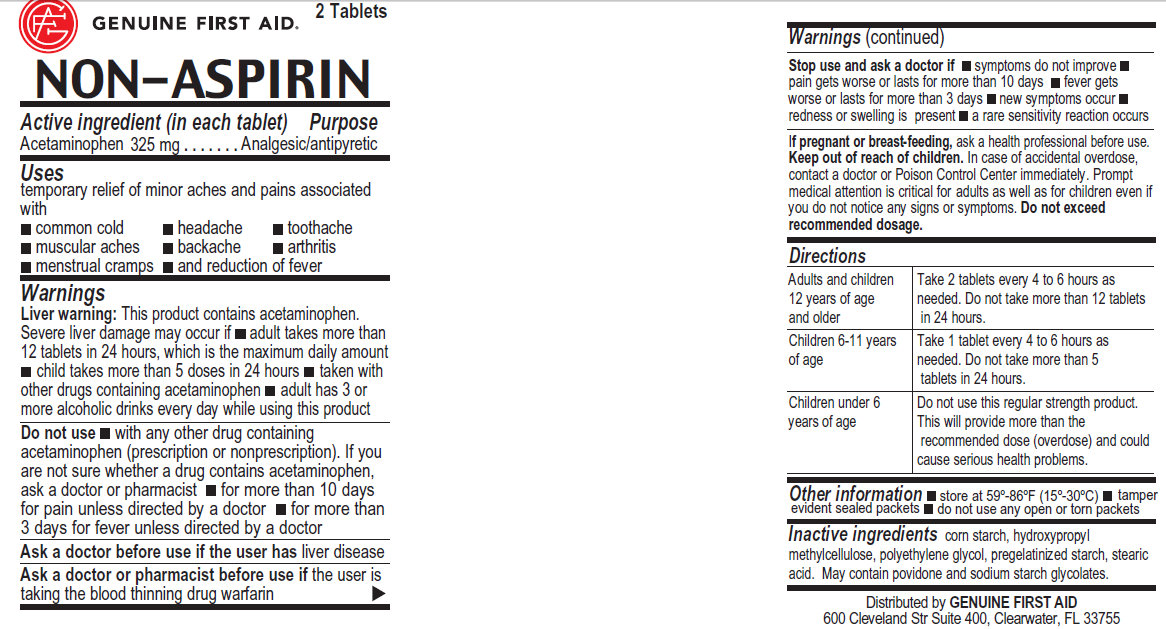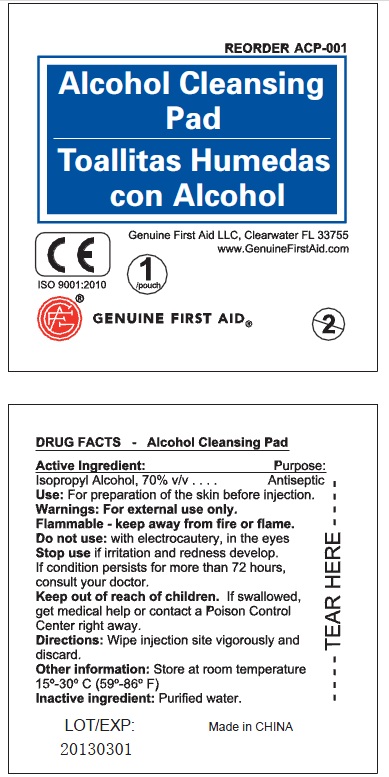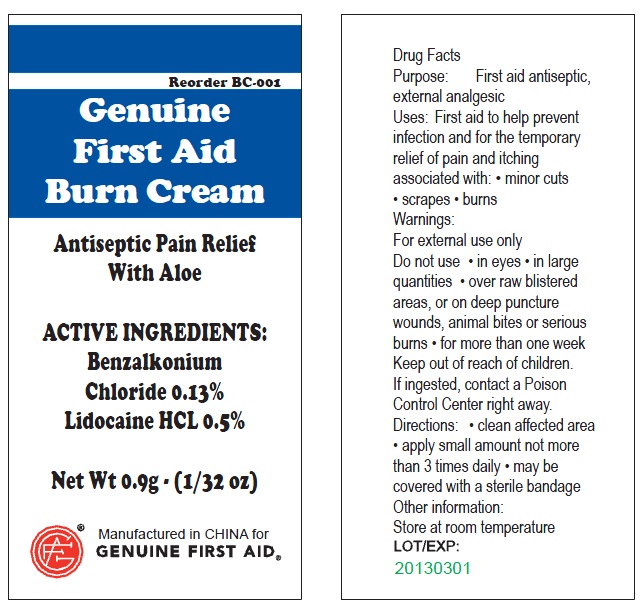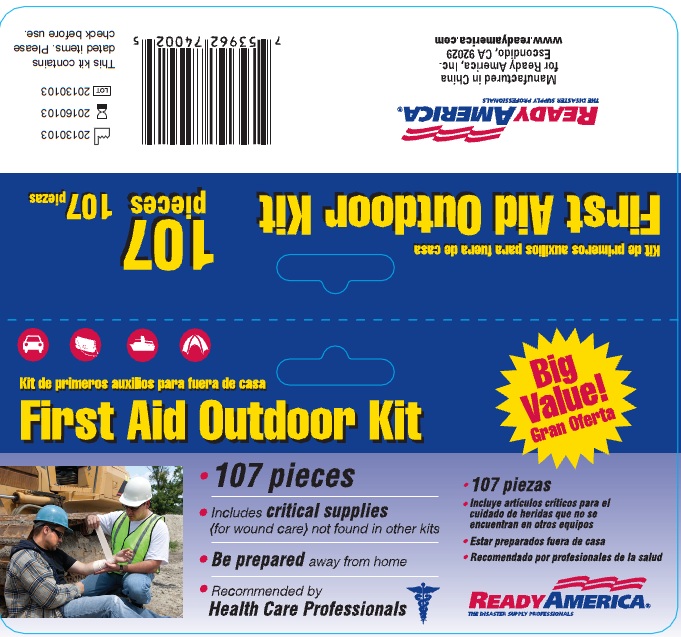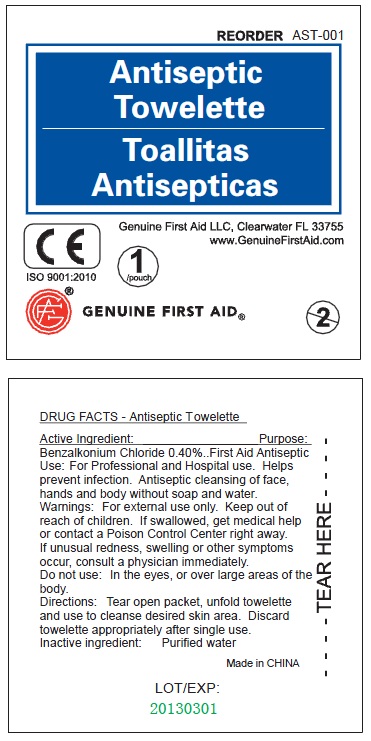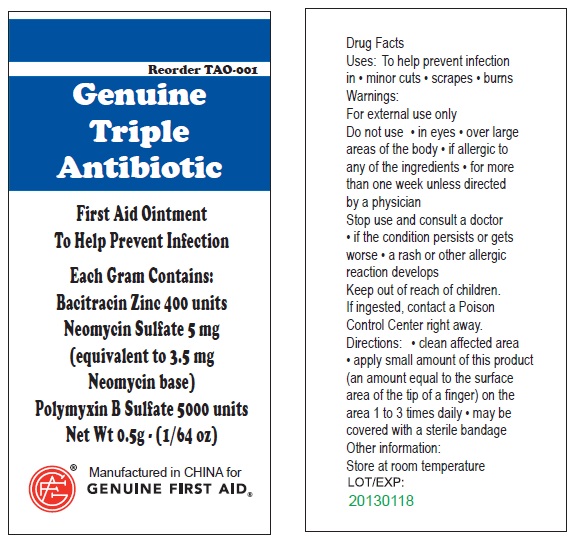 DRUG LABEL: Ready America First Aid Outdoor- 107 Pieces
NDC: 52124-4002 | Form: KIT | Route: TOPICAL
Manufacturer: Genuine First Aid, LLC
Category: otc | Type: HUMAN OTC DRUG LABEL
Date: 20130110

ACTIVE INGREDIENTS: BACITRACIN ZINC 400 [iU]/1 g; NEOMYCIN SULFATE 5 mg/1 g; POLYMYXIN B SULFATE 5000 [iU]/1 g; IBUPROFEN 200 mg/1 1; ACETAMINOPHEN 325 mg/1 1; ISOPROPYL ALCOHOL 70 mL/100 mL; ASPIRIN 325 mg/1 1; BENZALKONIUM CHLORIDE 1.3 mg/1 mL; BENZALKONIUM CHLORIDE 0.13 g/100 g; LIDOCAINE HYDROCHLORIDE 0.5 g/100 g; BENZOCAINE 0.6 mg/100 mL; ALCOHOL 60 mL/100 mL
INACTIVE INGREDIENTS: WATER; POWDERED CELLULOSE; STARCH, CORN; HYPROMELLOSES; LACTOSE; MAGNESIUM STEARATE; POLYDEXTROSE; POLYETHYLENE GLYCOLS; POVIDONE; SILICON DIOXIDE; STEARIC ACID; TITANIUM DIOXIDE; TRIACETIN; STARCH, CORN; POLYETHYLENE GLYCOLS; STEARIC ACID; POVIDONE; WATER; HYPROMELLOSES; POLYETHYLENE GLYCOLS; PROPYLENE GLYCOL; STARCH, CORN; WATER; ALOE VERA LEAF; CETYL ALCOHOL; DIAZOLIDINYL UREA; EDETATE DISODIUM; GLYCERIN; GLYCERYL MONOSTEARATE; METHYLPARABEN; MINERAL OIL; POLYETHYLENE GLYCOLS; PROPYLENE GLYCOL; PROPYLPARABEN; WATER; STEARIC ACID; WATER

Ready America First Aid Outdoor Kit 107 pcs

Active Ingredient: .........Bacitracin Zinc 400 units

Neomycin Sulfate 5mg (equivalent to 3.5 mg Neomycin base)

Polymyxin B Sulfate 5000 units

PURPOSE

Uses: To help prevent infection in:
minor cuts; scrapes; burns

Warnings:

For external use only.

Do not use: in eyes; over large areas of the body;

If allergic to any of the ingredients; for more than one week unless directed by a physician.

Stop use and consult a doctor:

if the condition persists or gets worse; a rash or other allergic reaction develops

Keep out of reach of children.

If ingested, contact a Poison

Control Center right away.

WHEN USING

Directions: clean affected area; apply small amount of this product (an amount equal to the surface area of the tip of a finger) on the area 1 to 3 times daily; may be covered with a sterile bandage

Other information:

Store at room temperature.

PACKAGE LABEL

Genuine Triple Antibiotic

First Aid Ointment

To Help Prevent Infection

Each Gram Contains:

Bacitracin Zinc 400 units

Neomycin Sulfate 5 mg

(equivalent to 3.5 mg

Neomycin base)

Polymyxin B Sulfate 5000 units

Net Wt. 0.5g ; (1/64 oz)

Manufactured in CHINA for

GENUINE FIRST AID.

Active ingredient (in each tablet) Purpose

Ibuprofen USP (NSAID*) 200mg . . . . . . . . . . . .Pain reliever/fever reducer

*nonsteroidal anti-inflammatory drug

PURPOSE

Uses temporarily relieves minor aches and pains due to:
the common cold
headache
toothache
muscular aches
backache
minor pain of arthritis
menstrual cramps temporarily reduces fever

Warnings

Allergy alert: Ibuprofen may cause a severe allergic reaction, especially in people allergic to aspirin. Symptoms may include: shock, facial swelling, asthma (wheezing) rash, skin reddening, blisters, hives If an allergic reaction occurs, stop use and seek medical help right away.

Stomach bleeding warning: This product contains a nonsteroidal anti-inflammatory drug (NSAID), which may cause severe stomach
bleeding. The chance is higher if you: are age 60 or older, have had stomach ulcers or bleeding problems, take a blood thinner (anticoagulant) or steroid drug, take other drugs containing NSAIDs (aspirin, ibuprofen, naproxen, or others), have 3 or more alcoholic drinks every day while using this product, take more or for a longer time than directed

Do not use if you have ever had an allergic reaction to any other pain reliever/fever reducer, right before or after heart surgery.

Ask a doctor before use if stomach bleeding warning applies to you; you have a history of stomach problems such as heartburn; you have a high blood pressure, heart disease, liver cirrhosis, or kidney disease; you are taking a diuretic

Ask a doctor before use if you are:
taking any other drug containing NSAID (prescription or nonprescription); taking aspirin for heart attack or stroke, because Ibuprofen may decrease this benefit of aspirin; taking any other drug

When using this product:
take with food or milk if stomach upset occurs

Stop use and ask a doctor If:
you experience any of the following signs of stomach bleeding; feel faint; vomit blood; have bloody or black stools; have stomach pain that does get better; pain gets worse or lasts more than 10 days; fever gets worse or lasts more than 3 days; redness or swelling is present in the painful area; any new symptoms appear

PREGNANCY OR BREAST FEEDING

If pregnant or breast-feeding, ask a health professional before use. It is especially important not to use ibuprofen during the last 3 months of pregnancy unless definitely directed to do so by a doctor because it may cause problems in the unborn child or complications during delivery.

Keep out of reach of children. In case of overdose, get medical help or contact a Poison Control Center right away.

Directions:
do not use more than directed; the smallest effective dose should be used; do not take longer than 10 days, unless directed by a doctor.
Adults and Children (12 years and older): Take 1 tablet every 4 to 6 hours while symptoms persist. If pain or fever does not respond to 1 tablet, 2 tablets may be used. Do not exceed 6 tablets in 24 hours, unless directed by a doctor.
Children under 12 years: Do not give to children under 12 years of age.

Other information: Store at controlled room temperature; avoid excessive heat 40 degree Celsius (104 degree Fahrenheit); tamper evident sealed packets; do not use any opened or torn packets

INACTIVE INGREDIENT

Inactive ingredients: cellulose, corn starch, fumed silica gel, hypromellose, lactose, magnesium stearate, polydextrose, polyethylene glycol, povidone, silica, sodium starch glycolate, stearic acid, titanium dioxide, triacetin.

DESCRIPTION

Distributed by GENUINE FIRST AID
600 Cleveland Str Suite 400, Clearwater, FL 33755

PACKAGE LABEL

IBUPROFEN 2 Tablets

Active Ingredient (in each tablet) Purpose

Aspirin (NSAID*) 325 mg............................... Pain Reliever / fever reducer

*nonsteroidal anti-inflammatory drug

PURPOSE

Uses Temporarily relieves minor aches and pains associated with:
headache ; muscular aches ; minor arthritis pain ; backache ; common cold ; toothache ; menstrual cramps ; Temporarily reduces fever

Warnings

Reye's syndrome: Children and teenagers who have or are recovering from chicken pox of flu-like symptoms should not use this product. When using this product, if changes in behavior with nausea and vomiting occur, consult a doctor because these symptoms could be an early sign of Reye's syndrome, a rare but serious illness.

Allergy alert: Aspirin may cause a severe allergic reaction which may include: hives, skin reddening, facial swelling, rash, asthma (wheezing), blisters, shock, If an allergic reaction occurs, stop use and seek medical help right away.

Stomach bleeding warning: This contains an NSAID, which may cause severe stomach bleeding. The chance is higher if you:
are age 60 or older; have had stomach ulcers or bleeding problems; take a blood thinner (anticoagulant) or steroid drug; take other drugs containing prescription or nonprescription NSAIDs (aspirin, ibuprofen, naproxen, or others); have 3 or more alcoholic drinks every day while using this product; take more or for a longer time than directed

Do not use: if you have ever had an allergic reaction to any other pain reliever/ fever reducer; right before or after heart surgery; if you are taking a prescription drug for gout, diabetes or arthritis

Ask a doctor before use if: stomach bleeding warning applies to you; you have a history of stomach problems such as heartburn; you have high blood pressure, heart disease, liver cirrhosis, or kidney disease; you are taking a diuretic

Ask a doctor or pharmacist before use if you are:

under a doctor's care for any serious condition; taking any other drug

When using this product: take with food or milk if stomach upset occurs

Stop use and ask a doctor if
you experience any of the following signs of stomach bleeding:
feel faint; vomit blood; have bloody or black stools; have stomach
pain that does not get better; pain gets worse or lasts more than 10 days; fever gets worse or lasts more than 3 days; you have difficulty swallowing; if ringing in the ears or loss of hearing occurs; redness or swelling is present in the painful areas; any new symptoms appear

PREGNANCY OR BREAST FEEDING

If pregnant or breast-feeding, ask a health professional before use. It is especially important to use aspirin during the last 3 months of pregnancy unless definitely directed to do so by a doctor because it may cause problems in the unborn child or complications during delivery.

Keep out of reach of children. In case of overdose, get medical help or

contact a Poison Control Center right away.

Directions

do not use more than directed

the smallest effective dose should be used

drink a full glass of water with each dose

do not take longer than 10 days, unless directed by a doctor

DOSAGE AND ADMINISTRATION

Adults and children: (12 years and older) Take 1 or 2 tablets with

water every 4 hours as needed. Do not take more than 12 tablets in 24

hours, or as directed by a doctor.

Children under 12 years: Do not give to children under 12 years of age.

STORAGE AND HANDLING

Store at 59 - 86 degree Fahrenheit (15 - 30 degree Celsius); avoid

excessive heat and humidity; tamper evident sealed packets;

Do not use any opened or torn packets

INACTIVE INGREDIENT

Inactive Ingredients: hypromellose, polyethylene glycol, propylene glycol, corn starch

DESCRIPTION

Distributed by GENUINE FIRST AID
600 Clevelad Str Suite 400, Clearwater, FL 33755

PACKAGE LABEL

ASPIRIN 2 Tablets

Active Ingredient: Purpose

Benzalkonium Chloride 0.40%.......... First Aid Antiseptic

PURPOSE

Use: For Professional and Hospital use. Helps prevent infection. Antiseptic cleansing of face, hands and body without soap and water.

WARNINGS

Warning: For external use only.

Keep out of reach of children: If swallowed, get medical help or contact a Poison Control Center right away.

Stop use if unusual redness, swelling or other symptoms occur. Consult a physician immediately.

Do not use in the eyes or over large areas of the body.

WHEN USING

Directions: Tear open packet, unfold towelette and use to cleanse desired skin area. Discard towelette appropriately after single use.

Inactive Ingredient: Purified water

DESCRIPTION

LOT/EXP: Made in CHINA

20130301

PACKAGE LABEL

Antiseptic Towelette

Genuine First Aid LLC, Clearwater FL 33755

www.GenuineFirstAid.com

1/pouch

GENUINE FIRST AID

Active Ingredient (in each tablet)

Acetaminophen 325 mg

Purpose

Analgesic/antipyretic

Uses

temporary relief of minor aches and pains associated with:

common cold; headache; toothache; muscular aches; backache; arthritis; menstrual cramps; and reduction of fever

Warnings

Liver warning: This product contains acetaminophen.

Severe liver damage may occur if: adult takes more than 12 tablets in 24 hours, which is the maximum daily amount; child takes more than 5 doses in 24 hours; taken with other drugs containing acetaminophen; adult has 3 or more alcoholic drinks every day while using this product

Do not use

with any other drug containing acetaminophen (prescription or nonprescription). If you are not sure whether a drug contains acetaminophen, ask a doctor or pharmacist; for more than 10 days for pain unless directed by a doctor; for more than 3 days for fever unless directed by a doctor

Ask a doctor before use if the user has liver disease

Ask a doctor or pharmacist before use if the user is taking the blood thinning drug warfarin

Stop use and ask a doctor if: symptoms do not improve; pain gets worse or lasts for more than 10 days; fever gets worse or lasts for more than 3 days; new symptoms occur; redness or swelling is present; a rare sensitivity reaction occurs

PREGNANCY OR BREAST FEEDING

If pregnant or breast-feeding, ask a health professional before use.

Keep out of reach of children. In case of accidental overdose, contact a doctor or Poison Control Center immediately. Prompt
medical attention is critical for adults as well as for children even if
you do not notice any signs or symptoms. Do not exceed recommended dosage

Inactive Ingredients

Cornstarch, polyethylene glycol, stearic acid, povidone

Directions

Adults and Children Take 2 tablets every 4 to 6 hours as

12 years of age needed. Do not take more than 12 tablets

or older in 24 hours.

Children 6-11 years Take 1 tablet every 4 to 6 hours as

of age needed. Do not take more than 5

tablets in 24 hours.

Children under 6 Do not use this regular strength product.

years of age This will provide more than the

recommended dose (overdose) and could

cause serious health problems.

STORAGE AND HANDLING

Store at 59-86 degree F (15-30 degree C)

GENERAL PRECAUTIONS

tamper evident sealed packets; do not use any open or torn packets

DESCRIPTION

Distributed by GENUINE FIRST AID
600 Cleveland Str Suite 400, Clearwater, FL 33755

PACKAGE LABEL

GENUINE FIRST AID 2 Tablets

NON-ASPIRIN

Active Ingredient

Isopropyl Alcohol, 70% v/v

Purpose

Antiseptic

Use

For preparation of skin before injection.

Warnings

For external use only.

STORAGE AND HANDLING

Flammable - keep away from fire or flame

Store at room temperature 15-30 degree Celsius (59-86 degree Fahrenheit)

Do not use: with electrocautery, in the eyes.

Stop use if irritation and redness develop. If condition persists for more than 72 hours, consult your doctor.

Keep out of reach of children. If swallowed,

get medical help or contact a Poison Control

Center right away.

Directions

Wipe Injection site vigorously and discard.

Inactive Ingredient

Purified water.

LOT/EXP: Made in CHINA

20140301

PACKAGE LABEL

Alcohol Cleansing Pad

Genuine First Aid LLC, Clearwater FL 33755

www.GenuineFirstAid.com

1/pouch

GENUINE FIRST AID

100 Alcohol cleansing pads

Reorder GFAP-39-02

Active Ingredients

Benzalkonium Chloride 0.13%
Lidocaine HCL 0.5%

Purpose

Purpose: First aid antiseptic, external analgesic

Uses

First aid to help prevent infection and for the temporary relief of pain and itching associated with:

Minor Cuts

Scrapes

Burns

Warnings

For external use only

Do not use: In eyes, in large quantities, over raw blistered areas, or on deep puncture wounds, animal bites or serious burns, for more than one week
Do not use:
in the eyes or apply over large areas of the body.
longer than 1 week unless directed by a doctor.
in large quantities, particularly over raw surfaces or blistered areas.
Ask a doctor before use if you have deep puncture wounds, animal bites or serious burns.
When using this product, avoid contact with the eyes.

Stop use and ask a doctor if
condition worsens
symptoms persist for more than 7 days
condition clears up and occurs again within a few days

Keep out of reach of Children.
If ingested, contact a Poison Control Center right away.

Directions

Adults and children 2 years of age and older

clean affected area.

apply a small amount of this product on the area 1 to 3 times daily.

may be covered with a sterile bandage

children under 2 years of age: consult a doctor

Other Information:
Store at room temperature (do not freeze).

Taper evident sealed packets.

Do not use packet if opened or torn.

Inactive Ingredients

Aloe vera, cetyl alcohol, diazolidinyl urea, edetate disodium, glycerin, glyceryl monostearate, methylparaben, mineral oil, polyethylene glycol, propylene glycol, propylparaben, purified water, stearic acid, irolamine

DESCRIPTION

LOT/EXP: Made in CHINA
20130301

GFA Production Xiamen Co., Ltd
No. 20 Huli Industrial Park, Meixi Road, Tong'an, Xiamen, Fujian, China 361100
Tel: 86-592-7269515 Fax: 86-592-7269528 Http: //www.gfaproduction.com

PACKAGE LABEL

Genuine First Aid Burn Cream
Antiseptic Pain Relief With Aloe
Net Wt 0.9g (1/32 oz)
Manufactured in CHINA for
Genuine First Aid.

Active Ingredient

Active Ingredient: Purpose:

Benzocaine, 6% w/v

SD alcohol, 60% w/v

Purpose

Topical Anesthetic
Antiseptic

Uses

Use: For the temporary relief of pain and itching associated with minor burns, scrapes and insect bites.

Directions

Clean intended area thoroughly with pad. Discard after single use.

Warnings

Warnings: For external use only.

Avoid contact with eyes. If this happens, rinse thoroughly with water.

Keep out of reach of children

If swallowed, get medical help or contact a Poison Control Center right away.

Inactive Ingredients

Purified water

STORAGE AND HANDLING

Flammable - keep away from fire or flame.

Do not use: In eyes, on broken skin, deep puncture wounds. If unusual redness, swelling, irritation or other symptoms occur, consult a physician immediately.

DESCRIPTION

Made in CHINA

LOT/EXP:

PACKAGE LABEL

Insect Sting Relief Pad

Genuine First Aid LLC, Clearwater FL 33755
www.GenuineFirstAid.com
1/pouch
GENUINE FIRST AID